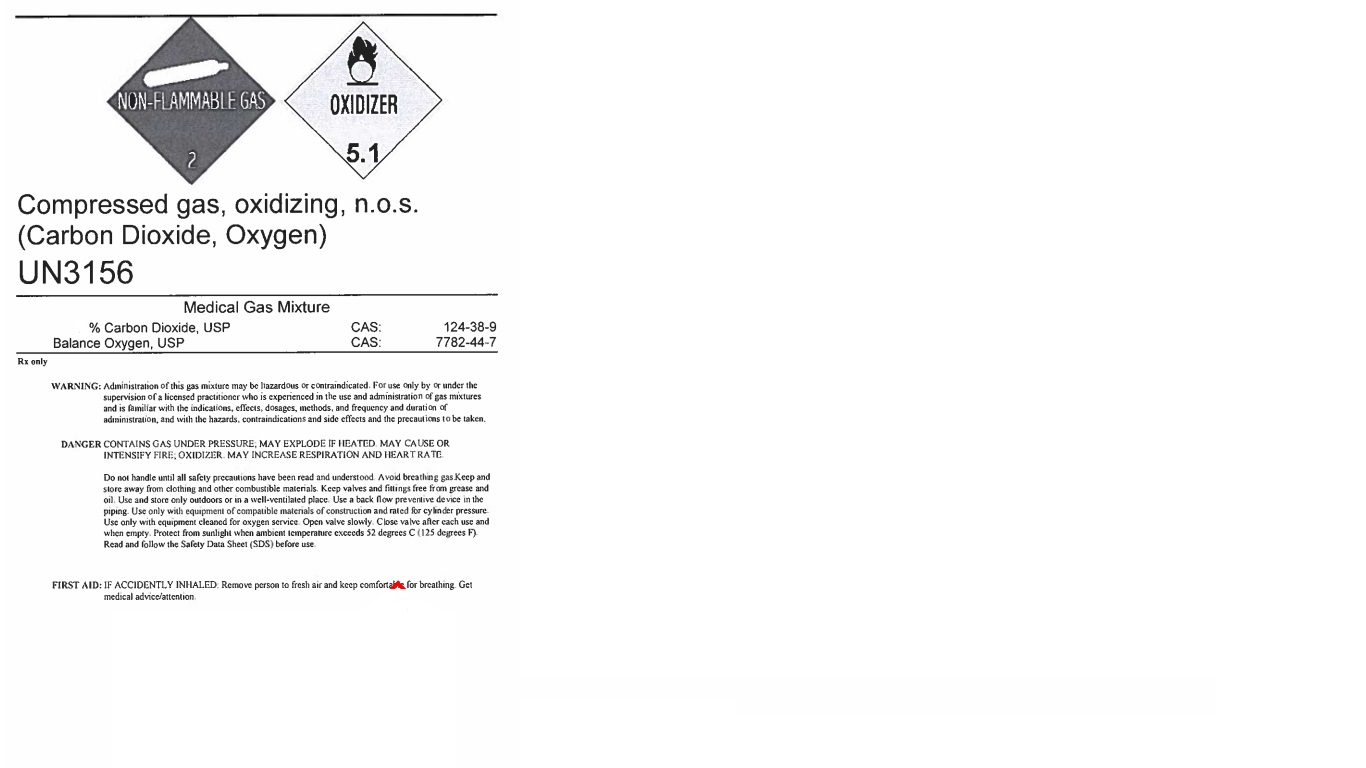 DRUG LABEL: Carbon Dioxide/Oxygen 5/95
NDC: 55037-702 | Form: GAS
Manufacturer: MATHESON TRI-GAS, INC.
Category: prescription | Type: HUMAN PRESCRIPTION DRUG LABEL
Date: 20251202

ACTIVE INGREDIENTS: OXYGEN 950 mL/1 L
INACTIVE INGREDIENTS: CARBON DIOXIDE 50 mL/1 L

Carbon Dioxide/Oxygen 5/95

PACKAGE LABEL

Compressed gas, oxidizing, n.o.s.

(Carbon Dioxide, Oxygen)

UN3156

Medical Gas Mixture

Carbon Dioxide, USP CAS: 124-38-9

Balance Oxygen, USP CAS: 7782-44-7

Rx only

WARNING: Administration of this gas mixture may be hazardous or contraindicated. For use only by or under the supervision of a licensed practitioner who is experienced in the use and administration of gas mixtures and is familiar with the indications, effects, dosages, methods, and frequency and duration of administration, and with the hazards, contraindications and side effects and the precautions to be taken.

DANGER CONTAINS GAS UNDER PRESSURE; MAY EXPLODE IF HEATED. MAY CAUSE OR INTENSIFY FIRE; OXIDIZER MAY INCREASE REPIRATION AND HEART RATE.

Do not handle until all safety precautions have been read and understood. Avoid breathing gas. Keep and store away from clothing and other combustible materials. Keep valves and fittings free from grease and oil. Use and store only outdoors or in a well-ventilated place. Use a back flow preventive device in the piping. Use only with equipment of compatible materials of construction and rated for cylinder pressure. Use only with equipment cleaned for oxygen service. Open valve slowly. Close valve after each use and when empty. Protect from sunlight when ambient temperature exceeds 52 degrees C (125 degrees F). Read and follow the Safety Data Sheet (SDS) before use.

FIRST AID: IF ACCIDENTLY INHALED: Remove person to fresh air and keep comfortable for breathing. Get medical advice/attention.

DO NOT REMOVE THIS PRODUCT LABEL

Matheson

909 Lake Carolyn Pkwy

Irving, TX 75039